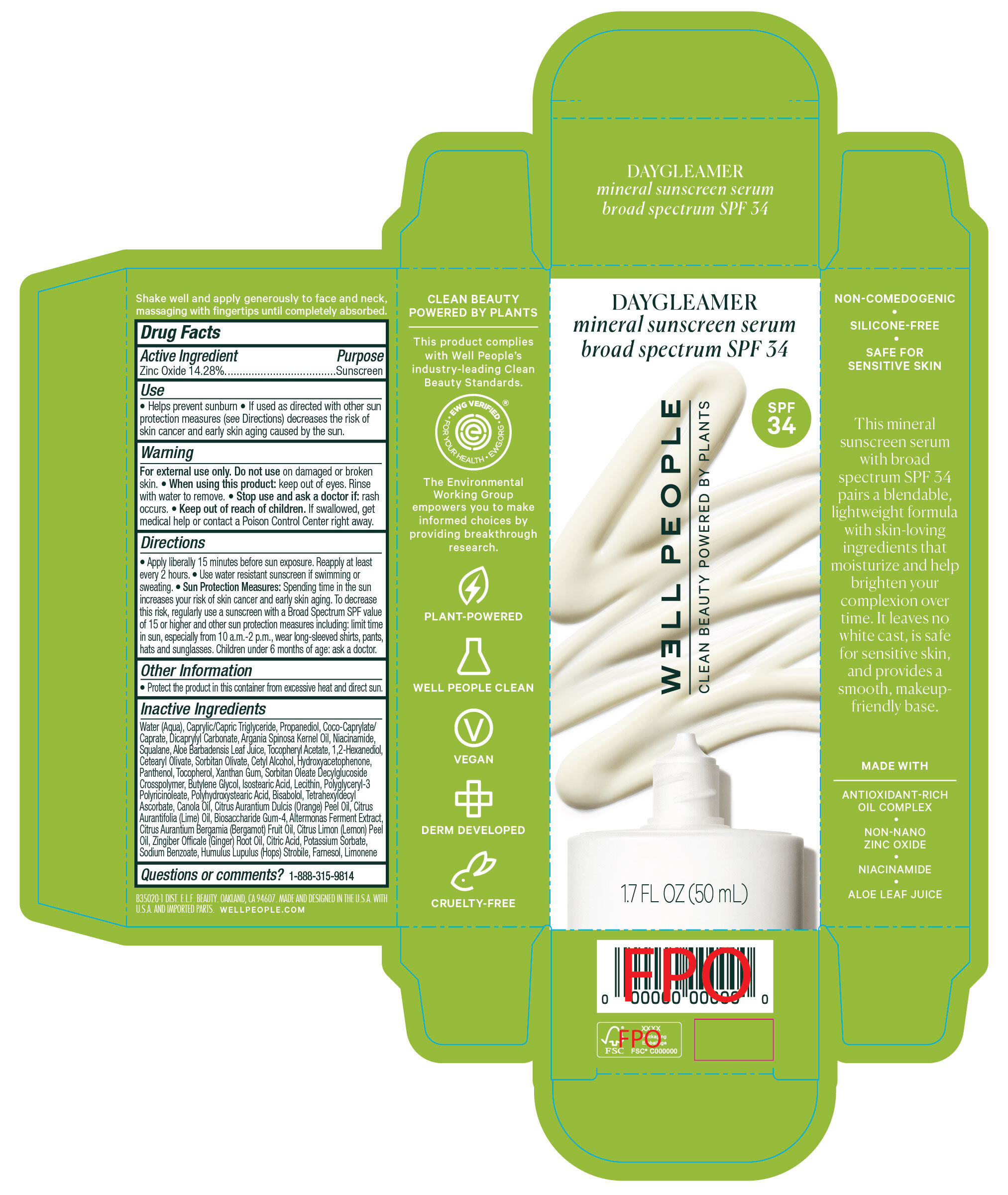 DRUG LABEL: Well People Daygleamer Liquid Mineral Sunscreen SPF 34
NDC: 76354-020 | Form: LOTION
Manufacturer: e.l.f. Cosmetics, Inc.
Category: otc | Type: HUMAN OTC DRUG LABEL
Date: 20250124

ACTIVE INGREDIENTS: ZINC OXIDE 142.8 mg/1 mL
INACTIVE INGREDIENTS: POTASSIUM SORBATE; BISABOLOL; CITRUS AURANTIUM DULCIS (ORANGE) PEEL OIL; TETRAHEXYLDECYL ASCORBATE; HYDROXYACETOPHENONE; PANTHENOL; XANTHAN GUM; LECITHIN, SOYBEAN; POLYGLYCERYL-3 RICINOLEATE; CITRIC ACID; FARNESOL; LIMONENE, (-)-; SORBITAN OLIVATE; CETYL ALCOHOL; CANOLA OIL; CITRUS AURANTIFOLIA (LIME) OIL; BIOSACCHARIDE GUM-4; CETEARYL OLIVATE; BUTYLENE GLYCOL; SODIUM BENZOATE; PROPANEDIOL; POLYHYDROXYSTEARIC ACID (2300 MW); WATER; DICAPRYLYL CARBONATE; ISOSTEARIC ACID; CITRUS LIMON (LEMON) PEEL OIL; ZINGIBER OFFICINALE (GINGER) ROOT OIL; .ALPHA.-TOCOPHEROL ACETATE, D-; 1,2-HEXANEDIOL; COCO-CAPRYLATE/CAPRATE; SQUALANE; SORBITAN OLEATE DECYLGLUCOSIDE CROSSPOLYMER; CAPRYLIC/CAPRIC TRIGLYCERIDE; ALOE BARBADENSIS LEAF JUICE; ARGANIA SPINOSA KERNEL OIL; NIACINAMIDE; TOCOPHEROL; ALTEROMONAS MACLEODII; HOPS; CITRUS AURANTIUM BERGAMIA (BERGAMOT) FRUIT OIL

Daygleamer Liquid Mineral Sunscreen SPF 34

Drug Facts

Active Ingredient

Zinc Oxide 14.28%

Purpose

Sunscreen

Uses

- Helps prevent sunburn
- If used as directed with other sun protection measures (see Directions) decreases the risk of skin cancer and early skin aging.

ACTIVE INGREDIENT

Zinc Oxide 14.28%

Warning

For external use only.

Do not use

on damaged or broken skin.

When using this product:

keep out of eyes. Rinse with water to remove.

Stop use and ask a doctor if:

rash occurs.

Keep out of reach of children

If swallowed, get medical help or contact a Poison Control Center right away.

Directions

- Apply liberally 15 minutes before sun exposure. Reapply at least every 2 hours.
- Use water resistant sunscreen if swimming or sweating.
- Sun Protection Measures: Spending time in the sun increases your risk of skin cancer and early skin aging. To decrease this risk, regularly use a sunscreen with a Broad Spectrum SPF value of 15 or higher and other sun protection measures including: limit time in sun, especially from 10a.m.-2 p.m., wear long-sleeved shirts, pants, hats and sunglasses. Children under 6 months of age: ask a doctor.

Other Information

Protect this product in this container from excessive heat and direct sun.

Inactive Ingredients

Water (Aqua), Caprylic/Capric Triglyceride, Propanediol, Coco-Caprylate/Caprate, Dicaprylyl Carbonate, Argania Spinosa Kernel Oil, Niacinamide, Squalane, Aloe Barbadensis Leaf Juice, Tocopheryl Acetate, 1,2-Hexanediol, Cetearyl Olivate, Sorbitan Olivate, Cetyl Alcohol, Hydroxyacetophenone, Panthenol, Tocopherol, Xanthan Gum, Sorbitan Oleate Decylglucoside Crosspolymer, Butylene Glycol, Isostearic Acid, Lecithin, Polyglyceryl-3 Polyricinoleate, Polyhydroxystearic Acid, Bisabolol, Tetrahexyldecyl Ascorbate, Canola Oil, Citrus Aurantium Dulcis (Orange) Peel Oil, Citrus Aurantifolia (Lime) Oil, Biosaccharide Gum-4, Altermonas Ferment Extract, Citrus Aurantium Bergamia (Bergamot) Fruit Oil, Citrus Limon (Lemon) Peel Oil, Zingiber Officale (Ginger) Root Oil, Citric Acid, Potassium Sorbate, Sodium Benzoate, Humulus Lupulus (Hops) Strobile, Farnesol, Limonene

Questions or Comments?

1-888-315-9814